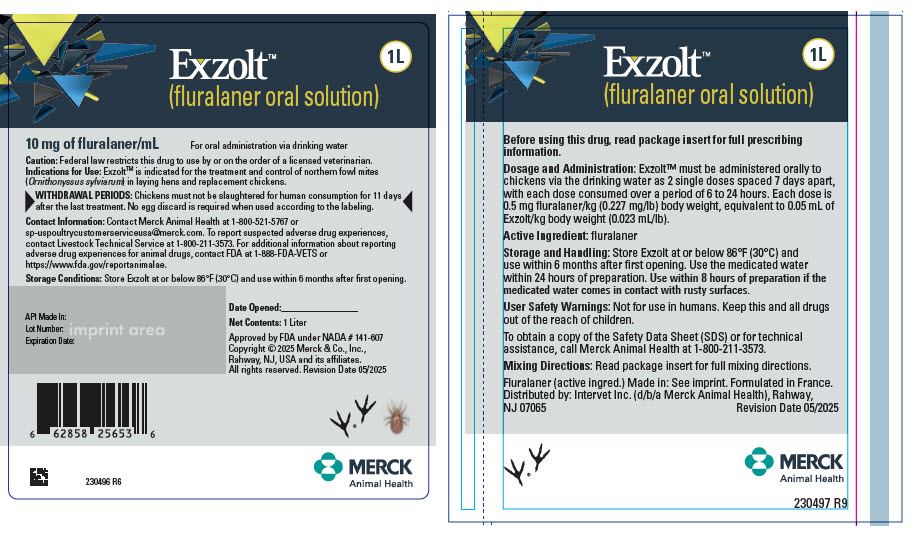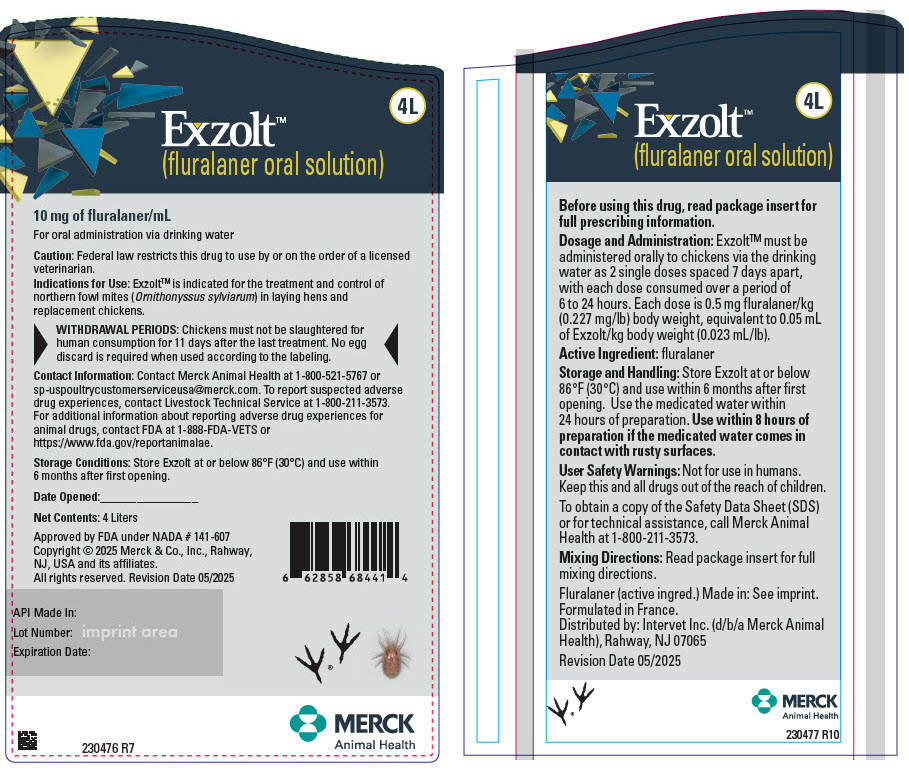 DRUG LABEL: Exzolt
NDC: 0061-1440 | Form: SOLUTION
Manufacturer: Merck Sharp & Dohme Corp.
Category: animal | Type: PRESCRIPTION ANIMAL DRUG LABEL
Date: 20250723

ACTIVE INGREDIENTS: FLURALANER 10 mg/1 L

Exzolt™ (fluralaner oral solution)

10 mg of fluralaner/mL

PRECAUTIONS

Caution: Federal law restricts this drug to use by or on the order of a licensed veterinarian.

DESCRIPTION

Description: Exzolt (fluralaner oral solution) is a concentrate for oral administration via drinking water containing fluralaner. Each mL of Exzolt contains 10 mg of fluralaner.

The chemical name of fluralaner is (±)-4-[5-(3,5-dichlorophenyl)-5-(trifluoromethyl)-4,5 dihydroisoxazol-3-yl]-2-methyl-N-[2-oxo-2-(2,2,2-trifluoroethylamino)ethyl] benzamide.

INDICATIONS AND USAGE

Indications for Use: Exzolt is indicated for the treatment and control of northern fowl mites (Ornithonyssus sylviarum) in laying hens and replacement chickens.

Dosage and Administration: Exzolt must be administered orally to chickens via the drinking water as 2 single doses spaced 7 days apart, with each dose consumed over a period of 6 to 24 hours. Each dose is 0.5 mg fluralaner/kg (0.227 mg/lb) body weight, equivalent to 0.05 mL of Exzolt/kg body weight (0.023 mL/lb).

General Mixing Directions: Determine the time period over which to administer the medicated water on the treatment day. This period of time must be a minimum of 6 hours and maximum of 24 hours and long enough to allow all birds to receive the required dose. If the medicated water will contact rusty surfaces, it must be consumed within 8 hours of preparation. Estimate how much water birds will usually consume during the selected treatment period based on the previous day's water consumption. Ensure that the amount of medicated drinking water offered will be consumed completely within the selected treatment period (between 6 and 24 hours). No other source of drinking water should be available during the medication period.

Calculate the volume of Exzolt needed based on the total weight of all birds in the house to be treated. To ensure administration of the correct dose, body weight should be estimated as accurately as possible and an accurate device should be used for measuring the calculated volume of product to be administered.

The required amount of Exzolt on each treatment day is calculated from the total body weight of the entire group of chickens to be treated:

Volume of Exzolt (mL) per treatment day = Total body weight (kg) of birds to be treated × 0.05 mL/kg
Or
Volume of Exzolt (mL) per treatment day = Total body weight (lb) of birds to be treated × 0.023 mL/lb

Examples:

Total body weight of birds to be treated | Volume of Exzolt per treatment day
5000 kg (11,023 lb) | 0.25 L (250 mL)
10,000 kg (22,046 lb) | 0.5 L (500 mL)
80,000 kg (176,370 lb) | 4 L
320,000 kg (705,479 lb) | 16 L

To prepare the medicated water, the instructions below need to be followed in the order described:

- Check the water system to ensure it works properly and is free of leaks; also ensure that water is available to all nipple or bell drinkers.
- For each day of treatment, medicated water must be freshly prepared.
  - Mix the required volume of the product into a large medication tank or create a stock solution in a small container. The stock solution must be further diluted with drinking water and administered over time, using a proportioner or dosing pump. Always add product and water simultaneously in order to avoid foaming. It is important to rinse the measuring device used to measure the required product volume during the filling phase in order to ensure that the complete dose is emptied into the medication tank or the stock solution and that no residues remain in the measuring device.
  - Stir the stock solution or the content of the medication tank gently until the medicated water is homogeneous. Connect the medication tank or the proportioner or dosing pump to the drinking water system.
- Make sure the dosing pump is properly set to deliver the medicated water during the predetermined treatment period (hours).
- Prior to introducing the medicated water, drain the drinker lines fully by opening the flush valve and checking end-line nipples to ensure no water remains.
- Prime the drinker lines with medicated water and confirm the medicated water has reached all end-line nipples.

Once the stock solution container is empty, rinse both the container and downstream water lines with unmedicated water (rinse water). Allow birds to consume the rinse water before reintroducing non-medicated water. The full course of therapy (2 single doses 7 days apart) must be administered for full therapeutic effect. Strict biosecurity measures at house and farm level should be implemented to prevent reinfestation of treated houses. To ensure long-term control of the mite populations in a treated house, it is essential to treat any other infested poultry in houses in proximity to the treated one.

Warnings

WITHDRAWAL PERIODS: Chickens must not be slaughtered for human consumption for 11 days after the last treatment. No egg discard is required when used according to the labeling.

User Safety Warnings: Not for use in humans. Keep this and all drugs out of the reach of children.

Protective gloves should be used. Care should be taken when handling the product to avoid skin and eye exposure, exposure of mucous membranes, and accidental ingestion. Accidental exposure may cause skin and eye irritation. In case of eye contact, immediately rinse thoroughly with water. If wearing contact lenses, immediately rinse the eyes first, then remove contact lenses and continue to rinse the eyes thoroughly. Seek medical advice if symptoms occur. Wash hands and contacted skin with soap and water after use of the product. Remove contaminated clothes and launder with detergent.

Accidental ingestion may cause gastrointestinal disturbances and hypersensitivity reactions in humans.

To obtain a copy of the Safety Data Sheet (SDS) or for technical assistance, call Merck Animal Health at 1-800-211-3573.

Contact Information: Contact Merck Animal Health at 1-800-521-5767 or sp-uspoultrycustomerserviceusa@merck.com. To report suspected adverse drug experiences, contact Livestock Technical Service at 1-800-211-3573. For additional information about reporting adverse drug experiences for animal drugs, contact FDA at 1-888-FDA-VETS or https://www.fda.gov/reportanimalae.

Clinical Pharmacology

Mechanism of Action: Fluralaner is for systemic use and belongs to the class of isoxazoline-substituted benzamide derivatives. Fluralaner acts as an inhibitor of the arthropod nervous system by antagonizing ligand-gated chloride channels (gamma-aminobutyric acid [GABA]-receptor and glutamate-receptor).

PHARMACOKINETICS

Pharmacokinetics: The pharmacokinetics of fluralaner were determined in fifty-five healthy laying hens treated with two single oral administrations of Exzolt (0.5 mg/kg twice) at 7-day intervals via drinking water. Concentrations of fluralaner peaked at 36 hours after the first administration and at 12 hours after the second administration. The maximum concentration (Cmax) of fluralaner was higher after the second dose (355 ng/mL) compared to after the first dose (323 ng/mL) suggesting slight accumulation. In a subsequent study, the oral bioavailability of fluralaner was determined in chickens after intravenous and oral administration (gavage) at a dose of 0.5 mg/kg. The oral bioavailability of fluralaner is 91%.

Target Animal Safety

Two margin of safety studies (growing broiler chickens and laying hens during peak egg production) and two reproductive safety studies (layer and broiler breeder chickens) were conducted.

The margin of safety study in broiler chickens was conducted in 320 3-week-old parent stock broiler chickens (Ross 308) at 1×, 3×, or 5× the recommended dose of 0.5 mg/kg body weight for 3 times the recommended duration at 7-day intervals, and the margin of safety study in laying hens was conducted in 120 commercial laying hens (Novogen) at 1×, 3×, or 5× the label dose for 3 consecutive days each, 7 days apart. No clinically relevant effects related to the administration of Exzolt were observed.

The reproductive safety study in layer chicken breeders was conducted in 432 (48 male and 384 female) commercial Bovans strain layer breeder chickens at 3 times the recommended dose on 4 occasions, 7 days apart and the reproductive safety study in broiler chicken breeders was conducted in 432 (48 male and 384 female) commercial Cobb 500 broiler breeder chickens at 3× the recommended dose on 4 occasions, 7 days apart. No clinically relevant effects on reproductive safety parameters related to the administration of Exzolt were observed.

These studies support the safety of Exzolt in laying hens and replacement chickens when administered in drinking water as 2 single doses of 0.5 mg/kg body weight, 7 days apart.

Effectiveness

In a well-controlled dose confirmation study conducted in 128 commercial 14-week-old White Leghorn female replacement chickens (Hy-Line® strain), effectiveness against Ornithonyssus sylviarum was 100% on Days 8, 14, 19, and 28 after the first treatment. No treatment-related adverse events were observed.

In a well-controlled dose confirmation study conducted in 128 commercial 29-week-old Brown Leghorn laying hens (Hy-Line strain), effectiveness against Ornithonyssus sylviarum was 100% on Days 8 and 14 after the first treatment. No treatment-related adverse events were observed.

In a well-controlled field effectiveness study conducted in 800 commercial 23-week-old White Leghorn laying hens (Hy-Line strain), effectiveness against Ornithonyssus sylviarum exceeded 99.9% on Days 8, 14, 19, and 28 after the first treatment. No treatment-related adverse events were observed.

In a well-controlled field effectiveness study conducted in 800 commercial 28-week-old White Leghorn (Hy-Line strain) laying hens, effectiveness against Ornithonyssus sylviarum exceeded 99.9% on Days 8, 14, 19, and 28 after the first treatment. No treatment-related adverse events were observed.

In all 4 effectiveness studies Exzolt achieved 99.3% or greater reduction in Ornithonyssus sylviarum mite counts on Day 2 following the first dose administration.

HOW SUPPLIED

How Supplied: Exzolt is available in 1- and 4-liter HDPE plastic containers.

Storage and Handling: Store Exzolt at or below 86°F (30°C) and use within 6 months after first opening. Use the medicated water within 24 hours of preparation. Use within 8 hours of preparation if the medicated water comes in contact with rusty surfaces.

Approved by FDA under NADA # 141-607

Distributed By: Intervet Inc. (d/b/a Merck Animal Health), 126 E. Lincoln Avenue, Rahway, NJ 07065

Copyright © 2025 Merck & Co., Inc., Rahway, NJ, USA and its affiliates. All rights reserved.

Revision Date 05/2025

PRINCIPAL DISPLAY PANEL - 1 Liter Bottle Label

Exzolt™
(fluralaner oral solution)

1L

10 mg of fluralaner/mL
For oral administration via drinking water

Caution: Federal law restricts this drug to use by or on the order of a licensed veterinarian.

Indications for Use: Exzolt™ is indicated for the treatment and control of northern fowl mites
(Ornithonyssus sylviarum) in laying hens and replacement chickens.

WITHDRAWAL PERIODS: Chickens must not be slaughtered for human consumption for 11 days
after the last treatment. No egg discard is required when used according to the labeling.

Contact Information: Contact Merck Animal Health at 1-800-521-5767 or
sp-uspoultrycustomerserviceusa@merck.com. To report suspected adverse drug experiences,
contact Livestock Technical Service at 1-800-211-3573. For additional information about reporting
adverse drug experiences for animal drugs, contact FDA at 1-888-FDA-VETS or
https://www.fda.gov/reportanimalae.

Storage Conditions: Store Exzolt at or below 86°F (30°C) and use within 6 months after first opening.

Date Opened:

Net Contents: 1 Liter

Approved by FDA under NADA # 141-607
Copyright © 2025 Merck & Co., Inc.,
Rahway, NJ, USA and its affiliates.
All rights reserved. Revision Date 05/2025

API Made In:

Lot Number:

Expiration Date:

230496 R6

MERCK
Animal Health

PRINCIPAL DISPLAY PANEL - 4 Liter Bottle Label

Exzolt™
(fluralaner oral solution)

4L

10 mg of fluralaner/mL

For oral administration via drinking water

Caution: Federal law restricts this drug to use by or on the order of a licensed
veterinarian.

Indications for Use: Exzolt™ is indicated for the treatment and control of
northern fowl mites (Ornithonyssus sylviarum) in laying hens and
replacement chickens.

WITHDRAWAL PERIODS: Chickens must not be slaughtered for
human consumption for 11 days after the last treatment. No egg
discard is required when used according to the labeling.

Contact Information: Contact Merck Animal Health at 1-800-521-5767 or
sp-uspoultrycustomerserviceusa@merck.com. To report suspected adverse
drug experiences, contact Livestock Technical Service at 1-800-211-3573.
For additional information about reporting adverse drug experiences for
animal drugs, contact FDA at 1-888-FDA-VETS or
https://www.fda.gov/reportanimalae.

Storage Conditions: Store Exzolt at or below 86°F (30°C) and use within
6 months after first opening.

Date Opened:

Net Contents: 4 Liters

Approved by FDA under NADA # 141-607
Copyright © 2025 Merck & Co., Inc., Rahway,
NJ, USA and its affiliates.
All rights reserved. Revision Date 05/2025

API Made In:

Lot Number:

Expiration Date:

230476 R7

MERCK
Animal Health